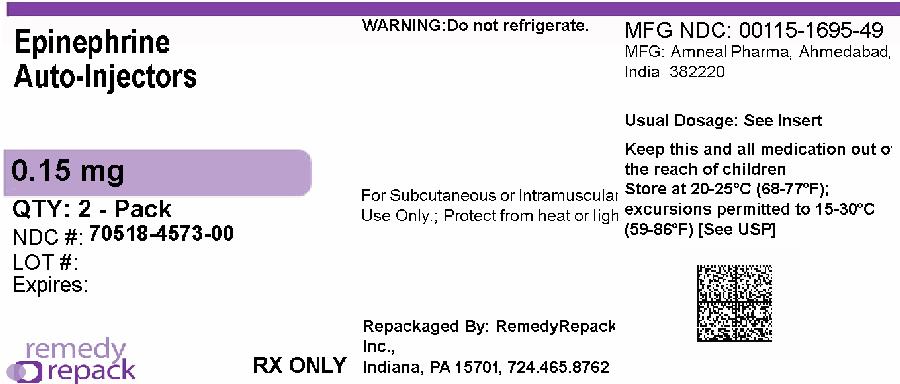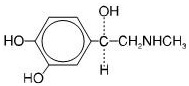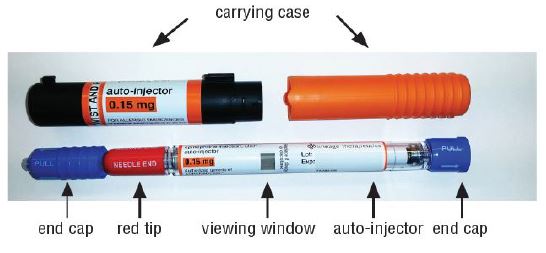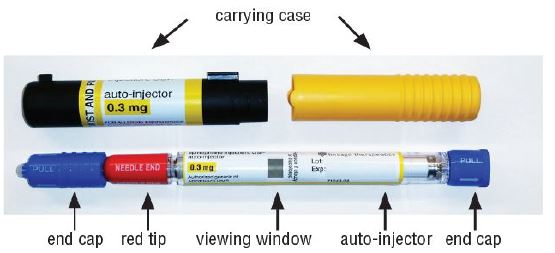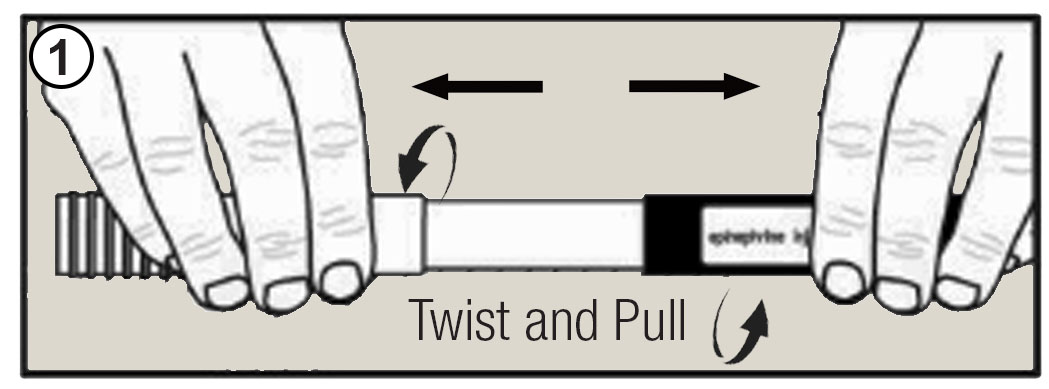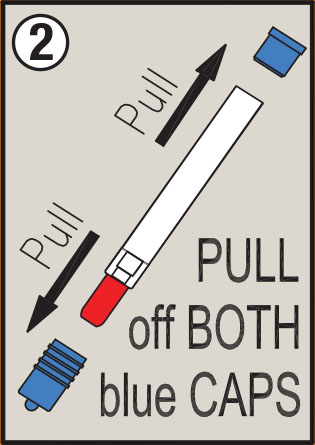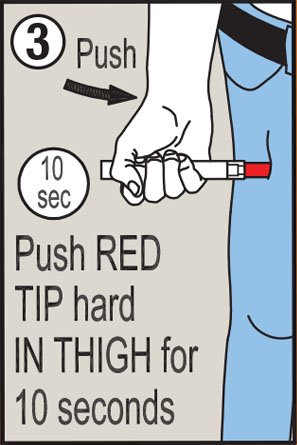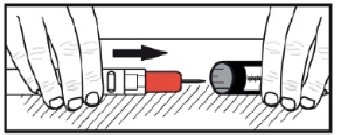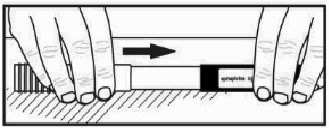 DRUG LABEL: epinephrine
NDC: 70518-4573 | Form: INJECTION
Manufacturer: REMEDYREPACK INC.
Category: prescription | Type: HUMAN PRESCRIPTION DRUG LABEL
Date: 20260218

ACTIVE INGREDIENTS: EPINEPHRINE 0.15 mg/0.15 mL
INACTIVE INGREDIENTS: SODIUM CHLORIDE; CHLOROBUTANOL; SODIUM BISULFITE; HYDROCHLORIC ACID; SODIUM HYDROXIDE

HIGHLIGHTS OF PRESCRIBING INFORMATION

These highlights do not include all the information needed to use EPINEPHRINE INJECTION safely and effectively. See full prescribing information for EPINEPHRINE INJECTION.
EPINEPHRINE injection, for intramuscular or subcutaneous use
Initial U.S. Approval: 1939

1 INDICATIONS AND USAGE

Epinephrine injection is a non-selective alpha and beta-adrenergic receptor agonist, indicated in the emergency treatment of allergic reactions (Type I) including anaphylaxis. (1)

2 DOSAGE AND ADMINISTRATION

- Patients greater than or equal to 30 kg (66 lbs): 0.3 mg (2)
- Patients 15 to 30 kg (33 lbs-66 lbs): 0.15 mg (2)

Inject intramuscularly or subcutaneously into the anterolateral aspect of the thigh, through clothing if necessary. Each device is a single-dose injection. (2)

3 DOSAGE FORMS AND STRENGTHS

- Injection: 0.15 mg (0.15 mg/0.15 mL) single-dose pre-filled auto-injector (3)

4 CONTRAINDICATIONS

None. (4)

5 WARNINGS AND PRECAUTIONS

- In conjunction with use, seek immediate medical or hospital care. (5.1)
- Do not inject intravenously, into buttock, or into digits, hands, or feet. (5.2)
- To minimize the risk of injection related injury, hold the child’s leg firmly in place and limit movement prior to and during injection when administering to young children. (5.2)
- Rare cases of serious skin and soft tissue infections have been reported following epinephrine injection. Advise patients to seek medical care if they develop signs or symptoms of infection. (5.3)
- The presence of a sulfite in this product should not deter use. (5.4)
- Administer with caution in patients with heart disease; may aggravate angina pectoris or produce ventricular arrhythmias. (5.5)

6 ADVERSE REACTIONS

Adverse reactions to epinephrine include anxiety, apprehensiveness, restlessness, tremor, weakness, dizziness, sweating, palpitations, pallor, nausea and vomiting, headache, and/or respiratory difficulties. (6)

To report SUSPECTED ADVERSE REACTIONS, contact Amneal Pharmaceuticals at 1-877-835-5472 or FDA at 1-800-FDA-1088 or www.fda.gov/medwatch.

7 DRUG INTERACTIONS

- Cardiac glycosides or diuretics: observe for development of cardiac arrhythmias. (7)
- Tricyclic antidepressants, monoamine oxidase inhibitors, levothyroxine sodium, and certain antihistamines: potentiate effects of epinephrine. (7)
- Beta-adrenergic blocking drugs: antagonize cardiostimulating and bronchodilating effects of epinephrine. (7)
- Alpha-adrenergic blocking drugs: antagonize vasoconstricting and hypertensive effects of epinephrine. (7)
- Ergot alkaloids: may reverse the pressor effects of epinephrine. (7)

8 USE IN SPECIFIC POPULATIONS

- Elderly patients may be at greater risk of developing adverse reactions. (5.5, 8.5)

FULL PRESCRIBING INFORMATION

1 INDICATIONS AND USAGE

Epinephrine injection is indicated in the emergency treatment of allergic reactions (Type I) including anaphylaxis to stinging insects (e.g., order Hymenoptera, which includes bees, wasps, hornets, yellow jackets and fire ants), and biting insects (e.g., triatoma, mosquitoes), allergen immunotherapy, foods, drugs, diagnostic testing substances (e.g., radiocontrast media), and other allergens, as well as idiopathic anaphylaxis or exercise-induced anaphylaxis.

Epinephrine injection is intended for immediate administration in patients who are determined to be at increased risk for anaphylaxis, including individuals with a history of anaphylactic reactions.

Anaphylactic reactions may occur within minutes after exposure and consist of flushing, apprehension, syncope, tachycardia, thready or unobtainable pulse associated with a fall in blood pressure, convulsions, vomiting, diarrhea and abdominal cramps, involuntary voiding, wheezing, dyspnea due to laryngeal spasm, pruritus, rashes, urticaria, or angioedema.

Epinephrine injection is intended for immediate administration as emergency supportive therapy only and is not a replacement or substitute for immediate medical care.

2 DOSAGE AND ADMINISTRATION

2.1 Recommended Dosage According to Patient Body Weight

- Patients greater than or equal to 30 kg (approximately 66 pounds or more): 0.3 mg
- Patients 15 kg to 30 kg (33 pounds to 66 pounds): 0.15 mg

2.2 Administration Instructions

- Inject the single-dose epinephrine injection intramuscularly or subcutaneously into the anterolateral aspect of the thigh, through clothing if necessary. Do not inject intravenously, and do not inject into buttocks, into digits, hands or feet [see Warnings and Precautions (5.2)].
- Instruct caregivers of young children who are prescribed an epinephrine injection and who may be uncooperative and kick or move during an injection to hold the leg firmly in place and limit movement prior to and during an injection [see Warnings and Precautions (5.2)].
- Each epinephrine injection is a single-dose of epinephrine injection for single use. Since the doses of epinephrine delivered from epinephrine injection are fixed, consider using other forms of injectable epinephrine if doses lower than 0.15 mg are deemed necessary.
- With severe persistent anaphylaxis, repeat injections with an additional epinephrine injection may be necessary. More than two sequential doses of epinephrine should only be administered under direct medical supervision [see Warnings and Precautions (5.1)].
- The epinephrine solution in the viewing window of epinephrine injection should be inspected visually for particulate matter and discoloration.

3 DOSAGE FORMS AND STRENGTHS

- Injection: 0.15 mg (0.15 mg/0.15 mL) of clear and colorless solution in single-dose pre-filled auto-injector

4 CONTRAINDICATIONS

None.

5 WARNINGS AND PRECAUTIONS

5.1 Emergency Treatment

Epinephrine injection is intended for immediate administration as emergency supportive therapy and is not intended as a substitute for immediate medical care. In conjunction with the administration of epinephrine, the patient should seek immediate medical or hospital care. More than two sequential doses of epinephrine should only be administered under direct medical supervision [see Indications and Usage (1), Dosage and Administration (2)and Patient Counseling Information (17)].

5.2 Injection-Related Complications

Epinephrine injection should onlybe injected into the anterolateral aspect of the thigh [see Dosage and Administration (2)and Patient Counseling Information (17)].

Do not inject intravenously

Large doses or accidental intravenous injection of epinephrine may result in cerebral hemorrhage due to a sharp rise in blood pressure. Rapidly acting vasodilators can counteract the marked pressor effects of epinephrine if there is such inadvertent administration.

Do not inject into buttock

Injection into the buttock may not provide effective treatment of anaphylaxis. Advise the patient to go immediately to the nearest emergency room for further treatment of anaphylaxis. Additionally, injection into the buttock has been associated with the development of Clostridial infections (gas gangrene). Cleansing with alcohol does not kill bacterial spores, and therefore, does not lower the risk.

Do not inject into digits, hands or feet

Since epinephrine is a strong vasoconstrictor, accidental injection into the digits, hands or feet may result in loss of blood flow to the affected area. Advise the patient to go immediately to the nearest emergency room and to inform the healthcare provider in the emergency room of the location of the accidental injection. Treatment of such inadvertent administration should consist of vasodilation, in addition to further appropriate treatment of anaphylaxis [see Adverse Reactions (6)].

Hold leg firmly during injection

Lacerations, bent needles, and embedded needles have been reported when epinephrine has been injected into the thigh of young children who are uncooperative and kick or move during an injection. To minimize the risk of injection related injury when administering, hold the child’s leg firmly in place and limit movement prior to and during injection.

5.3 Serious Infections at the Injection Site

Rare cases of serious skin and soft tissue infections, including necrotizing fasciitis and myonecrosis caused by Clostridia (gas gangrene), have been reported at the injection site following epinephrine injection for anaphylaxis. Clostridiumspores can be present on the skin and introduced into the deep tissue with subcutaneous or intramuscular injection. While cleansing with alcohol may reduce presence of bacteria on the skin, alcohol cleansing does not kill Clostridiumspores. To decrease the risk of Clostridiuminfection, do not inject epinephrine injection into the buttock [see Warnings and Precautions (5.2)]. Advise patients to seek medical care if they develop signs or symptoms of infection, such as persistent redness, warmth, swelling, or tenderness, at the epinephrine injection site.

5.4 Allergic Reactions Associated with Sulfite

The presence of a sulfite in this product should not deter administration of the drug for treatment of serious allergic or other emergency situations even if the patient is sulfite-sensitive.

Epinephrine is the preferred treatment for serious allergic reactions or other emergency situations even though this product contains sodium bisulfite, a sulfite that may, in other products, cause allergic-type reactions including anaphylactic symptoms or life-threatening or less severe asthmatic episodes in certain susceptible persons.

The alternatives to using epinephrine in a life-threatening situation may not be satisfactory.

5.5 Disease Interactions

Some patients may be at greater risk for developing adverse reactions after epinephrine administration. Despite these concerns, it should be recognized that the presence of these conditions is not a contraindication to epinephrine administration in an acute, life-threatening situation. Therefore, patients with these conditions, and/or any other person who might be in a position to administer epinephrine injection to a patient experiencing anaphylaxis should be carefully instructed in regard to the circumstances under which epinephrine should be used.

Patients with Heart Disease

Epinephrine should be administered with caution to patients who have heart disease, including patients with cardiac arrhythmias, coronary artery or organic heart disease, or hypertension. In such patients, or in patients who are on drugs that may sensitize the heart to arrhythmias, epinephrine may precipitate or aggravate angina pectoris as well as produce ventricular arrhythmias [see Drug Interactions (7)and Adverse Reactions (6)].

Other Patients and Diseases

Epinephrine should be administered with caution to patients with hyperthyroidism, diabetes, elderly individuals, and pregnant women. Patients with Parkinson’s disease may notice a temporary worsening of symptoms.

6 ADVERSE REACTIONS

Due to the lack of randomized, controlled clinical trials of epinephrine for the treatment of anaphylaxis, the true incidence of adverse reactions associated with the systemic use of epinephrine is difficult to determine. Adverse reactions reported in observational trials, case reports, and studies are listed below.

Common adverse reactions to systemically administered epinephrine include anxiety; apprehensiveness; restlessness; tremor; weakness; dizziness; sweating; palpitations; pallor; nausea and vomiting; headache; and/or respiratory difficulties. These symptoms occur in some persons receiving therapeutic doses of epinephrine, but are more likely to occur in patients with hypertension or hyperthyroidism [see Warnings and Precautions (5.5)].

Cardiovascular Reactions

- Arrhythmias, including fatal ventricular fibrillation, have been reported, particularly in patients with underlying cardiac disease or those receiving certain drugs [see Warnings and Precautions (5.5)and Drug Interactions (7)].
- Rapid rises in blood pressure have produced cerebral hemorrhage, particularly in elderly patients with cardiovascular disease [see Warnings and Precautions (5.5)].
- Angina may occur in patients with coronary artery disease [see Warnings and Precautions (5.5)].
- Rare cases of stress cardiomyopathy have been reported in patients treated with epinephrine.

Reactions from Accidental Injection and/or Improper Technique

- Accidental injection into the digits, hands or feet may result in loss of blood flow to the affected area [see Warnings and Precautions (5.2)].

- Adverse reactions experienced as a result of accidental injections may include increased heart rate, local reactions including injection site pallor, coldness and hypoesthesia or injury at the injection site resulting in bruising, bleeding, discoloration, erythema or skeletal injury.
- Lacerations, bent needles, and embedded needles have been reported when epinephrine injection has been injected into the thigh of young children who are uncooperative and kick or move during an injection [see Warnings and Precautions (5.2)].
- Injection into the buttock has resulted in cases of gas gangrene [see Warnings and Precautions (5.2)].

Skin and Soft Tissue Infections

- Rare cases of serious skin and soft tissue infections, including necrotizing fasciitis and myonecrosis caused by Clostridia (gas gangrene), have been reported following epinephrine injection in the thigh [see Warnings and Precautions (5.3)].

7 DRUG INTERACTIONS

Cardiac Glycosides, Diuretics, and Anti-arrhythmics

Patients who receive epinephrine while concomitantly taking cardiac glycosides, diuretics, or anti-arrhythmics should be observed carefully for the development of cardiac arrhythmias [see Warnings and Precautions (5.5)].

Antidepressants, Monoamine Oxidase Inhibitors, Levothyroxine, and Antihistamines

The effects of epinephrine may be potentiated by tricyclic antidepressants, monoamine oxidase inhibitors, levothyroxine sodium, and certain antihistamines, notably chlorpheniramine, tripelennamine, and diphenhydramine.

Beta-Adrenergic Blockers

The cardiostimulating and bronchodilating effects of epinephrine are antagonized by beta- adrenergic blocking drugs, such as propranolol.

Alpha-Adrenergic Blockers

The vasoconstricting and hypertensive effects of epinephrine are antagonized by alpha-adrenergic blocking drugs, such as phentolamine.

Ergot Alkaloids

Ergot alkaloids may also reverse the pressor effects of epinephrine.

8 USE IN SPECIFIC POPULATIONS

8.1 Pregnancy

Risk Summary

There are no available human data on the use of epinephrine injection in pregnant women to inform a drug-associated risk of adverse developmental outcomes. In animal reproduction studies, epinephrine administered by the subcutaneous route to rabbits, mice, and hamsters during the period of organogenesis was teratogenic at doses 7 times and higher than the maximum recommended daily subcutaneous or intramuscular dose on a mg/m^2basis (see Data). Epinephrine is the first-line medication of choice for the treatment of anaphylaxis during pregnancy in humans. Epinephrine should be used for treatment of anaphylaxis during pregnancy in the same manner as it is used in non-pregnant patients.

In the U.S. general population, the estimated background risk of major birth defects and miscarriage in clinically recognized pregnancies is 2 to 4% and 15 to 20%, respectively.

Clinical Considerations

Disease-associated maternal and embryo/fetal risk:

During pregnancy, anaphylaxis can be catastrophic and can lead to hypoxic-ischemic encephalopathy and permanent central nervous system damage or death in the mother and, more commonly, in the fetus or neonate. The prevalence of anaphylaxis occurring during pregnancy is reported to be approximately 3 cases per 100,000 deliveries.

Management of anaphylaxis during pregnancy is similar to management in the general population. Epinephrine is the first line-medication of choice for treatment of anaphylaxis; it should be used in the same manner in pregnant and non-pregnant patients. In conjunction with the administration of epinephrine, the patient should seek immediate medical or hospital care.

Data

Animal Data

In an embryofetal development study with rabbits dosed during the period of organogenesis, epinephrine was shown to be teratogenic (including gastroschisis and embryonic lethality) at doses approximately 40 times the maximum recommended intramuscular or subcutaneous dose (on a mg/m^2basis at a maternal subcutaneous dose of 1.2 mg/kg/day for two to three days).

In an embryofetal development study with mice dosed during the period of organogenesis, epinephrine was shown to be teratogenic (including embryonic lethality) at doses approximately 8 times the maximum recommended intramuscular or subcutaneous dose (on a mg/m^2basis at maternal subcutaneous dose of 1 mg/kg/day for 10 days). These effects were not seen in mice at approximately 4 times the maximum recommended daily intramuscular or subcutaneous dose (on a mg/m^2basis at a subcutaneous maternal dose of 0.5 mg/kg/day for 10 days).

In an embryofetal development study with hamsters dosed during the period of organogenesis from gestation days 7 to 10, epinephrine was shown to be teratogenic at doses approximately 7 times the maximum recommended intramuscular or subcutaneous dose (on a mg/m^2basis at a maternal subcutaneous dose of 0.5 mg/kg/day).

8.2 Lactation

Risk Summary

There are no data on the presence of epinephrine in human milk, or the effects of epinephrine on the breastfed infant or on milk production. Epinephrine is the first line-medication of choice for treatment of anaphylaxis; it should be used in the same manner in breastfeeding and no-breastfeeding patients.

8.4 Pediatric Use

Epinephrine injection may be administered to pediatric patients at a dosage appropriate to body weight [see Dosage and Administration (2.1)]. Clinical experience with the use of epinephrine suggests that the adverse reactions seen in children are similar in nature and extent to those both expected and reported in adults. Since the dose of epinephrine delivered from epinephrine injection is fixed, consider using other forms of injectable epinephrine if doses lower than 0.15 mg are deemed necessary.

8.5 Geriatric Use

Clinical studies for the treatment of anaphylaxis have not been performed in subjects aged 65 and over to determine whether they respond differently from younger subjects. However, other reported clinical experience with use of epinephrine for the treatment of anaphylaxis has identified that geriatric patients may be particularly sensitive to the effects of epinephrine. Therefore, epinephrine injection should be administered with caution in elderly individuals, who may be at greater risk for developing adverse reactions after epinephrine administration [see Warnings and Precautions (5.5) and Overdosage (10)].

10 OVERDOSAGE

Overdosage of epinephrine may produce extremely elevated arterial pressure, which may result in cerebrovascular hemorrhage, particularly in elderly patients. Overdosage may also result in pulmonary edema because of peripheral vascular constriction together with cardiac stimulation. Treatment consists of a rapidly acting vasodilators or alpha-adrenergic blocking drugs and/or respiratory support.

Epinephrine overdosage can also cause transient bradycardia followed by tachycardia, and these may be accompanied by potentially fatal cardiac arrhythmias. Premature ventricular contractions may appear within one minute after injection and may be followed by multifocal ventricular tachycardia (prefibrillation rhythm). Subsidence of the ventricular effects may be followed by atrial tachycardia and occasionally by atrioventricular block. Treatment of arrhythmias consists of administration of a beta-adrenergic blocking drug such as propranolol.

Overdosage sometimes results in extreme pallor and coldness of the skin, metabolic acidosis, and kidney failure. Suitable corrective measures must be taken in such situations.

11 DESCRIPTION

Epinephrine injection, USP 0.3 mg and 0.15 mg is an auto-injector and a combination product containing drug and device components.

Each epinephrine injection, USP 0.3 mg delivers a single dose of 0.3 mg epinephrine from epinephrine injection, USP (0.3 mL) in a sterile solution.

Each epinephrine injection, USP 0.15 mg delivers a single dose of 0.15 mg epinephrine from epinephrine injection, USP (0.15 mL) in a sterile solution.

Epinephrine injection, USP 0.3 mg and epinephrine injection, USP 0.15 mg each contain 1.1 mL of epinephrine solution. 0.3 mL and 0.15 mL epinephrine solution are dispensed for epinephrine injection, USP 0.3 mg and epinephrine injection, USP 0.15 mg, respectively, when activated. The solution remaining after activation is not available for future use and should be discarded.

Each 0.3 mL in epinephrine injection, USP 0.3 mg contains 0.3 mg epinephrine, 2.6 mg sodium chloride, not more than 1.5 mg chlorobutanol, 0.45 mg sodium bisulfite, hydrochloric acid and sodium hydroxide to adjust pH, and water for injection. The pH range is 2.2-5.0.

Each 0.15 mL in epinephrine injection, USP 0.15 mg contains 0.15 mg epinephrine, 1.3 mg sodium chloride, not more than 0.75 mg chlorobutanol, 0.225 mg sodium bisulfite, hydrochloric acid and sodium hydroxide to adjust pH, and water for injection. The pH range is 2.2-5.0.

Epinephrine is a sympathomimetic catecholamine. Chemically, epinephrine is (-)-3,4-Dihydroxy-α-[(methylamino)methyl]benzyl alcohol with the following structure:

Epinephrine solution deteriorates rapidly on exposure to air or light, turning pink from oxidation to adrenochrome and brown from the formation of melanin. Replace epinephrine injection, USP if the epinephrine solution appears discolored (pinkish or brown color), cloudy, or contains particles.

Thoroughly review the patient instructions and operation of epinephrine injection, USP with patients and caregivers prior to use [see Patient Counseling Information (17) ].

12 CLINICAL PHARMACOLOGY

12.1 Mechanism of Action

Epinephrine acts on both alpha- and beta-adrenergic receptors.

12.2 Pharmacodynamics

Through its action on alpha-adrenergic receptors, epinephrine lessens the vasodilation and increased vascular permeability that occurs during anaphylaxis, which can lead to loss of intravascular fluid volume and hypotension.

Through its action on beta-adrenergic receptors, epinephrine causes bronchial smooth muscle relaxation and helps alleviate bronchospasm, wheezing, and dyspnea that may occur during anaphylaxis.

Epinephrine also alleviates pruritus, urticaria, and angioedema, and may relieve gastrointestinal and genitourinary symptoms associated with anaphylaxis because of its relaxer effects on the smooth muscle of the stomach, intestine, uterus and urinary bladder.

When given intramuscularly or subcutaneously, epinephrine has a rapid onset and short duration of action.

13 NONCLINICAL TOXICOLOGY

13.1 Carcinogenesis, Mutagenesis, Impairment of Fertility

Long-term studies to evaluate the carcinogenic potential of epinephrine have not been conducted.

Epinephrine and other catecholamines have been shown to have mutagenic potential in vitro. Epinephrine was positive in the Salmonella bacterial reverse mutation assay, positive in the mouse lymphoma assay, and negative in the in vivo micronucleus assay. Epinephrine is an oxidative mutagen based on the E. coli WP2 Mutoxitest bacterial reverse mutation assay. This should not prevent the use of epinephrine where indicated under the conditions noted under [see Indications and Usage (1)].

The potential for epinephrine to impair reproductive performance has not been evaluated, but epinephrine has been shown to decrease implantation in female rabbits dosed subcutaneously with 1.2 mg/kg/day (40-fold the highest human intramuscular or subcutaneous daily dose) during gestation days 3 to 9.

16 HOW SUPPLIED/STORAGE AND HANDLING

Carton containing two epinephrine injection, USP 0.15 mg single-dose pre-filled auto-injectors

NDC: 70518-4573-00

OUTER PACKAGING: 2 in 1 CARTON

INNER PACKAGING: 1 in 1 CASE

PACKAGING: 0.15 mL in 1 SYRINGE, GLASS TYPE 2

Storage and Handling

Protect from light. Epinephrine is light sensitive and should be stored in the carrying-case provided to protect it from light. Store at room temperature (20°C to 25°C (68°F to 77°F)); excursions permitted to 15°C to 30°C (59°F to 86°F) [See USP Controlled Room Temperature]. Do not refrigerate. Before using, check to make sure the solution in the auto-injector is clear and colorless. Replace the auto-injector if the solution is discolored (pinkish or brown color), cloudy, or contains particles.

Properly dispose of all used, unwanted, or expired epinephrine injection, USP.

Repackaged and Distributed By:

Remedy Repack, Inc.

625 Kolter Dr. Suite #4 Indiana, PA 1-724-465-8762

17 PATIENT COUNSELING INFORMATION

See FDA-Approved Patient Labeling (Patient Information and Instructions for Use)

A healthcare provider should review the patient instructions and operation of epinephrine injection, in detail, with the patient or caregiver.

Epinephrine is essential for the treatment of anaphylaxis. Carefully instruct patients who are at risk of or with a history of severe allergic reactions (anaphylaxis) to insect stings or bites, foods, drugs, and other allergens, as well as idiopathic and exercise-induced anaphylaxis, about the circumstances under which epinephrine should be used.

Administration

Instruct patients and/or caregivers in the appropriate use of epinephrine injection. Epinephrine injection should be injected into the middle of the outer thigh (through clothing if necessary).

Instruct caregivers to hold the leg of young children firmly in place and limit movement prior to and during injection. Lacerations, bent needles, and embedded needles have been reported when epinephrine injection has been injected into the thigh of young children who are uncooperative and kick during an injection [see Warnings and Precautions (5.2)].

Advise patients to seek immediate medical care in conjunction with administration of epinephrine injection.

Complete patient information, including dosage, directions for proper administration and precautions can be found inside each epinephrine injection carton. A printed label on the surface of epinephrine injection shows instructions for use and a diagram depicting the injection process.

Training

Instruct patients and/or caregivers to use the Trainer to familiarize themselves with the use of epinephrine injection in an allergic emergency. The Trainer may be used multiple times.

Adverse Reactions

Epinephrine may produce symptoms and signs that include an increase in heart rate, the sensation of a more forceful heartbeat, palpitations, sweating, nausea and vomiting, difficulty breathing, pallor, dizziness, weakness or shakiness, headache, apprehension, nervousness, or anxiety. These signs and symptoms usually subside rapidly, especially with rest, quiet, and recumbency. Patients with hypertension or hyperthyroidism may develop more severe or persistent effects, and patients with coronary artery disease could experience angina. Patients with diabetes may develop increased blood glucose levels following epinephrine administration. Patients with Parkinson’s disease may notice a temporary worsening of symptoms [see Warnings and Precautions (5.5)].

Accidental Injection

Advise patients to seek immediate medical care in the case of accidental injection. Since epinephrine is a strong vasoconstrictor when injected into the digits, hands or feet, treatment should be directed at vasodilation if there is such an accidental injection to these areas [see Warnings and Precautions (5.2)].

Serious Infections at the Injection Site

Rare cases of skin and soft tissue infections, including necrotizing fasciitis and myonecrosis caused by Clostridia (gas gangrene), have been reported at the injection site following epinephrine injection for anaphylaxis. Advise patients to seek medical care if they develop signs or symptoms of infection, such as persistent redness, warmth, swelling, or tenderness, at the epinephrine injection site [see Warnings and Precautions (5.3)].

Pregnancy and Breastfeeding

Inform patients that epinephrine injection has not been studied in pregnant women or breastfeeding mothers so the effects of epinephrine injection on pregnant women or breastfed infants are not known. Instruct patients to tell their healthcare provider if they are pregnant, become pregnant, or are thinking about becoming pregnant. Instruct patients to tell their healthcare provider if they plan to breastfeed their infant [see Use in Specific Populations (8.1, 8.2)].

Storage and Handling

Instruct patients to inspect the epinephrine solution visually through the viewing window periodically. Replace epinephrine injection if the epinephrine solution appears discolored (pinkish or brown), cloudy, or contains particles. Epinephrine is light sensitive, store in the outer case provided to protect it from light. Instruct patients that epinephrine injection must be properly disposed of once the blue caps have been removed or after use [see How Supplied/Storage and Handling (16)].

Complete patient information, including dosage, directions for proper administration and precautions are provided inside each epinephrine injection carton.

Repackaged By / Distributed By: RemedyRepack Inc.

625 Kolter Drive, Indiana, PA 15701

(724) 465-8762

PATIENT INFORMATION

EPINEPHRINE injection (ep-in-eph-rine),

for intramuscular or subcutaneous use

For allergic emergencies (anaphylaxis)

Read this Patient Information leaflet carefully before you use epinephrine injection and each time you get a refill. There may be new information. You, your parent, caregiver, or others who may be in a position to administer epinephrine injection should know how to use it before you have an allergic emergency.

This information does not take the place of talking with your healthcare provider about your medical condition or your treatment.

What is the most important information I should know about epinephrine injection?

1. Epinephrine injection contains epinephrine, a medicine used to treat allergic emergencies (anaphylaxis). Anaphylaxis can be life-threatening, can happen within minutes, and can be caused by stinging and biting insects, allergy injections, foods, medicines, exercise, or other unknown causes. Symptoms of anaphylaxis may include:

- trouble breathing
- wheezing
- hoarseness (changes in the way your voice sounds)
- hives (raised reddened rash that may itch)
- severe itching
- swelling of your face, lips, mouth, or tongue
- skin rash, redness, or swelling
- fast heartbeat
- weak pulse
- feeling very anxious
- confusion
- stomach pain
- losing control of urine or bowel movements (incontinence)
- diarrhea or stomach cramps
- dizziness, fainting, or “passing out” (unconsciousness)

2. Always carry your epinephrine injection with you because you may not know when anaphylaxis may happen.Talk to your healthcare provider if you need additional units to keep at work, school, or other locations. Tell your family members, caregivers, and others where you keep your epinephrine injection and how to use it before you need it. You may be unable to speak in an allergic emergency.

3. When you have an allergic emergency (anaphylaxis)

- Use epinephrine injection right away.
- Get emergency medical help right away.You may need further medical attention. You may need to use a second epinephrine injection if symptoms continue or recur. Only a healthcare provider should give additional doses of epinephrine if you need more than 2 injections for a single anaphylaxis episode.

What is epinephrine injection?

- Epinephrine injection is a disposable, prefilled automatic injection device (auto-injector) used to treat life-threatening, allergic emergencies including anaphylaxis in people who are at risk for or have a history of serious allergic emergencies. Each device contains a single dose of epinephrine.
- Epinephrine injection is for immediate self (or caregiver) administration and does not take the place of emergency medical care. You should get emergency medical help right away after using epinephrine injection.
- Epinephrine injection is for people who have been prescribed this medicine by their healthcare provider.
- The epinephrine injection 0.3 mg auto-injector is for patients who weigh 66 pounds or more (30 kilograms or more).
- The epinephrine injection 0.15 mg auto-injector is for patients who weigh about 33 to 66 pounds (15 to 30 kilograms).
- It is not known if epinephrine injection is safe and effective in children who weigh less than 33 pounds (15 kilograms).

Before using epinephrine injection, tell your healthcare provider about all your medical conditions, especially if you:

- have heart problems or high blood pressure
- have diabetes
- have thyroid problems
- have asthma
- have a history of depression
- have Parkinson's disease
- are pregnant or plan to become pregnant. It is not known if epinephrine will harm your unborn baby.
- are breastfeeding or plan to breastfeed. It is not known if epinephrine passes into your breast milk.

Tell your healthcare provider about all the medicines you take,including prescription and over-the-counter medicines, vitamins and herbal supplements. Tell your healthcare provider of all known allergies.

Especially tell your healthcare provider if you take certain asthma medicines.

Epinephrine injection and other medicines may affect each other, causing side effects. Epinephrine injection may affect the way other medicines work, and other medicines may affect how epinephrine injection works.

Know the medicines you take. Keep a list of them to show your healthcare provider and pharmacist when you get a new medicine.

Use your epinephrine injection for treatment of anaphylaxis as prescribed by your healthcare provider, regardless of your medical conditions or the medicine you take.

How should I use epinephrine injection?

- Each epinephrine injection contains only 1 dose of medicine.
- Epinephrine injection should only be injected into the middle of the outer thigh (upper leg). It can be injected through clothing if needed.
- Read the Instructions for Use at the end of this Patient Information Leaflet for information about the right way to use epinephrine injection.
- Your healthcare provider will show you how to safely use epinephrine injection.
- Use epinephrine injection exactly as your healthcare provider tells you to use it. You may need to use a second epinephrine injection if symptoms continue or recur. Only a healthcare provider should give additional doses of epinephrine if you need more than 2 injections for a single anaphylaxis episode.
- Caution: Never put your thumb, fingers, or hand over the red tip. Never press or push the red tip with your thumb, fingers, or hand.The needle comes out of the red tip. Accidental injection into finger, hands, or feet may cause a loss of blood flow to those areas. If this happens, go immediately to the nearest emergency room.Tell the healthcare provider where on your body you received the accidental injection.
- Your epinephrine injection comes packaged in a carton containing 1 or 2 epinephrine injections.
- You may request a separate Trainer, that comes packaged with instructions. Additional video instructions on the use of epinephrine injection are available from www.epinephrineautoinject.com. The epinephrine injection Trainer has a beige color. The beige epinephrine injection Trainer contains no medicine and no needle.Practice with your epinephrine injection Trainer before an allergic emergency happens to make sure you are able to safely use the real epinephrine injection in an emergency. Always carry your real epinephrine injection, USP auto-injector with you in case of an allergic emergency.
- Do not drop the carrying case or epinephrine injection. If the carrying case or epinephrine injection is dropped, check for damage and leakage. Throw away (dispose of) epinephrine injection and the carrying case, and replace if damage or leakage is noticed or suspected.

What are the possible side effects of epinephrine injection?

Epinephrine injection may cause serious side effects.

- Epinephrine injection should only be injected into the middle of your outer thigh (upper leg). Do notinject epinephrine injection into your:
  - veins
  - buttocks
  - fingers, toes, hands or feet.

If you accidentally inject epinephrine injection into any other part of your body, go to the nearest emergency room right away. Tell the healthcare provider where on your body you received the accidental injection.

- Rarely, people who have used epinephrine injection may develop infections at the injection site within a few days of an injection.Some of these infections can be serious. Call your healthcare provider right away if you have any of the following at an injection site:
  - redness that does not go away
  - swelling
  - tenderness
  - the area feels warm to the touch
- Cuts on the skin, bent needles, and needles that remain in the skin after the injection, have happened in young children who do not cooperate and kick or move during an injection. If you inject a young child with epinephrine injection, hold their leg firmly in place before and during the injection to prevent injuries. Ask your healthcare provider to show you how to properly hold the leg of a young child during an injection.
- If you have certain medical conditions, or take certain medicines, your condition may get worse or you may have more or longer lasting side effects when you use epinephrine injection.Talk to your healthcare provider about all your medical conditions.

Common side effects of epinephrine injection include:

- faster, irregular or “pounding” heartbeat
- sweating
- headache
- weakness
- shakiness
- paleness
- feelings of over excitement, nervousness, or anxiety
- dizziness
- nausea and vomiting
- breathing problems

These side effects may go away with rest. Tell your healthcare provider if you have any side effect that bothers you or that does not go away.

These are not all the possible side effects of epinephrine injection. For more information, ask your healthcare provider or pharmacist.

Call your doctor for medical advice about side effects. You may report side effects to FDA at 1-800-FDA-1088.

How should I store epinephrine injection?

- Store epinephrine injection at room temperature between 68°F to 77° F (20°C to 25° C).
- Protect from light.
- Do notexpose to extreme heat or cold. For example, do notstore in your vehicle’s glove box and do notstore in the refrigerator or freezer.
- Examine the contents in the viewing window of your epinephrine injection periodically. The solution should be clear. If the solution is discolored (pinkish or brown), cloudy or contains solid particles, replace the unit.
- Always keep your epinephrine injection in the carrying case to protect it from damage. The carrying case is not waterproof.
- The two blue end caps help to prevent accidental injection. Do not remove the blue end caps until you are ready to use epinephrine injection.
- Your epinephrine injection has an expiration date. Replace it before the expiration date.
- Throw away (dispose of) expired, unwanted, or unused epinephrine injections in an FDA-cleared sharps disposal container. Do not throw away epinephrine injection in your household trash. If you do not have an FDA-cleared sharps disposal container, you may use a household container that is:
  - Made of heavy-duty plastic,
  - Can be closed with a tight-fitting, puncture-resistant lid, without sharps being able to come out,
  - Upright and stable during use,
  - Leak-resistant, and
  - Properly labeled to warn of hazardous waste inside the container.
  When your sharps disposal container is almost full, you will need to follow your community guidelines for the right way to dispose of your sharps disposal container. There may be state or local laws about how you should throw away used needles and syringes. For more information about safe sharps disposal, and for specific information about sharps disposal in the state that you live in, go to the FDA’s website at: http://www.fda.gov/safesharpsdisposal. Visit the FDA’s website (https://www.fda.gov/drugs/safe-disposal-medicines/disposal- unused-medicines-what-you-should-know) for more information about how to throw away (dispose of) unused, unwanted or expired medicines.

Keep epinephrine injection and all medicines out of the reach of children.

General information about the safe and effective use of epinephrine injection:

Medicines are sometimes prescribed for purposes other than those listed in a Patient Information leaflet. Do not use epinephrine injection for a condition for which it was not prescribed. Do not give epinephrine injection to other people.

This Patient Information leaflet summarizes the most important information about epinephrine injection. If you would like more information, talk to your healthcare provider. You can ask your pharmacist or healthcare provider for information about epinephrine injection that is written for health professionals.

What are the ingredients in epinephrine injection?

Active Ingredient:epinephrine

Inactive Ingredients:sodium chloride, chlorobutanol, sodium bisulfite, hydrochloric acid and sodium hydroxide, and water.

For more information and video instructions on the use of epinephrine injection, go to www.epinephrineautoinject.com or call 1-877-835-5472.

Important Information

- The epinephrine injection, 0.3 mg auto-injector has a yellow colored label.
- The epinephrine injection, 0.15 mg auto-injector has an orange colored label.
- The epinephrine injection Trainer has a beige color, and contains no medicine and no needle.
- Your epinephrine injection is designed to work through clothing.
- The two blue end caps on epinephrine injection help to prevent accidental injection of the device. Do not remove the two blue end caps until you are ready to use it.
- Only inject into the middle of the outer thigh (upper leg). Never inject into any other part of the body.
- Never put your thumb, fingers, or your hand over the red tip. The needle comes out of the red tip.
- If an accidental injection happens, get medical help right away.
- Do not place patient information or any other foreign objects in carrier with the auto-injector, as this may prevent you from removing epinephrine injection for use.

This Patient Information has been approved by the U.S. Food and Drug Administration Rev. 02-2021-04

Instructions for Use

EPINEPHRINE injection (ep-in-eph-rine)

for intramuscular or subcutaneous use

For allergic emergencies (anaphylaxis)

Read this Instructions for Use carefully before you use epinephrine injection and each time you get a refill. There may be new information. Before you need to use your epinephrine injection, make sure your healthcare provider shows you the right way to use it. Parents, caregivers, and others who may be in a position to administer epinephrine injection should also understand how to use it well. This information does not take the place of talking to your healthcare provider about your medical condition or your treatment. If you have any questions, ask your healthcare provider.

Your epinephrine injection

Step 1. Prepare epinephrine injection, for injection

- Remove epinephrine injection from its protective carrying case. See Figure A.

Figure A

- Pull off blue end caps. You will now see a red tip. Grasp the epinephrine injection in your fist with the red tip pointing downward. See Figure B.

Note:

- The needle comes out of the red tip.
- To avoid an accidental injection, never put your thumb, fingers, or hand over the red tip. If an accidental injection happens, get medical help right away.

Figure B

S tep2. Administer epinephrine injection

- If you are administering epinephrine injection to a young child, hold the leg firmly in place and limit movement prior to and while administering an injection.
- Place the red tip against the middle of the outer thigh(upper leg) at a 90° angle (perpendicular) to the thigh.
- Press down hardand hold firmly against the thigh for approximately 10 secondsto deliver the medicine. See Figure C.

Figure C

- Only inject into the middle of the outer thigh. Do notinject into any other part of the body.
- Remove epinephrine injection from the thigh.
- Massage the area for 10 seconds.
- Check the red tip.The injection is complete and you have received the correct dose of the medicine if you see the needle sticking out of the redtip. If you do not see the needle repeat Step 2.

S tep3. Get emergency medical help right away. You may need further medical attention. You may need to use a second epinephrine injection if symptoms continue or recur.

S tep4. After use Disposal

Carefully cover the needle with the carrying case.

- Lay the labeled half of the carrying case cover down on a flat surface. Use one hand to carefully slide the end of epinephrine injection, needle first, into the labeled carrying case cover. See Figure D.

Figure D

- After the needle is inside the labeled cover, push the unlabeled half of the carrying case cover firmly over the non-needle end of the epinephrine injection. See Figure E.

Figure E

- Take your used epinephrine injection with you when you go to see a healthcare provider.
- Tell the healthcare provider that you have received an injection of epinephrine. Show the healthcare provider where you received the injection.
- Give your used epinephrine injection to the healthcare provider for inspection and proper disposal.
- Ask for a refill, if needed.

Note:

- Epinephrine injection is a single-use injectable device that delivers a fixed dose of epinephrine. Epinephrine injection cannot be reused. Do not attempt to reuse epinephrine injection after the device has been activated. It is normal for most of the medicine to remain in the auto-injector after the dose is injected. The correct dose has been administered if you see the needle sticking out of the redtip.
- A separate epinephrine injection Trainer is available. The epinephrine injection Trainer has a beige color. The beige epinephrine injection Trainer contains no medicine and no needle. Practice with your epinephrine injection Trainer, but always carry your real epinephrine injection in case of an allergic emergency.
- If you will be administering epinephrine injection to a young child, ask your healthcare provider to show you how to properly hold the leg in place while administering a dose.
- Do not try to take epinephrine injection apart.

For more information and video instructions on the use of epinephrine injection, go to www.epinephrineautoinject.com or call 1-877-835-5472.

This Patient Information and Instructions for Use has been approved by the U.S. Food and Drug Administration.

© 2021 Amneal Pharmaceuticals LLC. All rights reserved.

Repackaged and Distributed By:

Remedy Repack, Inc.

625 Kolter Dr. Suite #4 Indiana, PA 1-724-465-8762

Revised 10-2024-05

PRINCIPAL DISPLAY PANEL

DRUG: epinephrine

GENERIC: epinephrine

DOSAGE: INJECTION

ADMINSTRATION: SUBCUTANEOUS

NDC: 70518-4573-0

PACKAGING: 0.15 mL in 1 SYRINGE, GLASS

MIDDLE PACKAGING: 1 in 1 CASE

OUTER PACKAGING: 2 in 1 CARTON

ACTIVE INGREDIENT(S):

- EPINEPHRINE 0.15mg in 0.15mL

INACTIVE INGREDIENT(S):

- SODIUM CHLORIDE
- CHLOROBUTANOL
- SODIUM BISULFITE
- HYDROCHLORIC ACID
- SODIUM HYDROXIDE